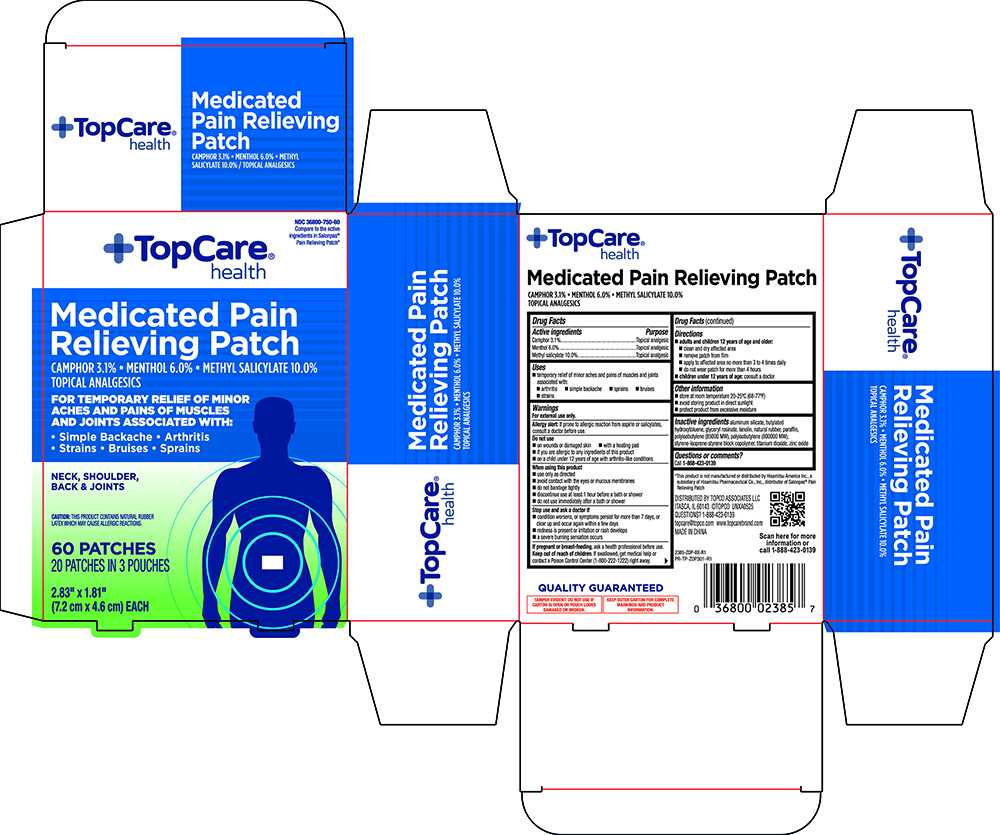 DRUG LABEL: Topcare Medicated Pain Relieving Patch 60ct
NDC: 36800-750 | Form: PATCH
Manufacturer: Topco Associates LLC
Category: otc | Type: HUMAN OTC DRUG LABEL
Date: 20260126

ACTIVE INGREDIENTS: MENTHOL 60 mg/1 g; CAMPHOR (SYNTHETIC) 31 mg/1 g; METHYL SALICYLATE 100 mg/1 g
INACTIVE INGREDIENTS: LANOLIN; GLYCERYL ROSINATE; ZINC OXIDE; POLYISOBUTYLENE (800000 MW); STYRENE/ISOPRENE/STYRENE BLOCK COPOLYMER; BUTYLATED HYDROXYTOLUENE; ALUMINUM SILICATE; POLYISOBUTYLENE (85000 MW); TITANIUM DIOXIDE; NATURAL LATEX RUBBER; PARAFFIN

Topcare 2385 Medicated Pain Relieving Patch 60ct

Active ingredients Purpose
Camphor 3.1%............................................................Topical analgesic
Menthol 6.0%..............................................................Topical analgesic
Methyl salicylate 10.0%...............................................Topical analgesic

Uses
 temporary relief of minor aches and pains of muscles and joints
associated with:
 arthritis  simple backache  sprains  bruises
 strains

Warnings
For external use only.

Do not use
 on wounds or damaged skin  with a heating pad
 if you are allergic to any ingredients of this product
 on a child under 12 years of age with arthritis-like conditions

Allergy alert: If prone to allergic reaction from aspirin or salicylates,
consult a doctor before use.

When using this product
 use only as directed
 avoid contact with the eyes, or mucous membranes
 do not bandage tightly
 discontinue use at least 1 hour before a bath or shower
 do not use immediately after a bath or shower

Stop use and ask a doctor if
 condition worsens, or symptoms persist for more than 7 days, or
clear up and occur again within a few days
 redness is present or irritation or rash develops
 a severe burning sensation occurs

PREGNANCY OR BREAST FEEDING

If pregnant or breast-feeding, ask a health professional before use.

Keep out of reach of children. If swallowed, get medical help or
contact a Poison Control Center (1-800-222-1222) right away.

Directions
 adults and children 12 years of age and older:
 clean and dry affected area
 remove patch from film
 apply to affected area no more than 3 to 4 times daily
 do not wear patch for more than 4 hours
 children under 12 years of age: consult a doctor

Other information
 store at room temperature 20-25ºC (68-77º)
 avoid storing product in direct sunlight
 protect product from excessive moisture

Inactive ingredients aluminum silicate, butylated
hydroxytoluene, glyceryl rosinate, lanolin, natural rubber, paraffin,
polyisobutylene (85000 MW), polyisobutylene (800000 MW),
styrene-isoprene-styrene block copolymer, titanium dioxide, zinc oxide

Questions or comments?

Call 1-888-423-0139

Distributed By TOPCO ASSOCIATES LLC

ITASCA, IL 60143 @TOPCO UNXA0525

Questions? 1-888-423-0139

opcare@topco.com www.topcarebrand.com

MADE IN CHINA